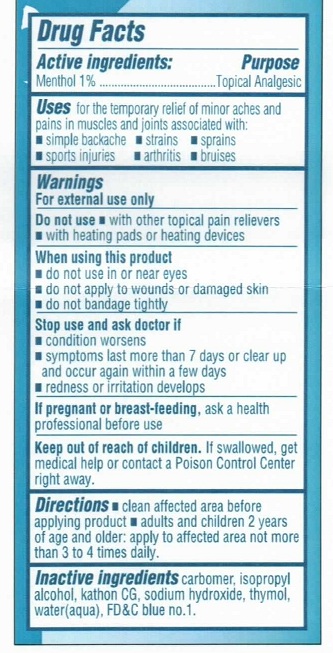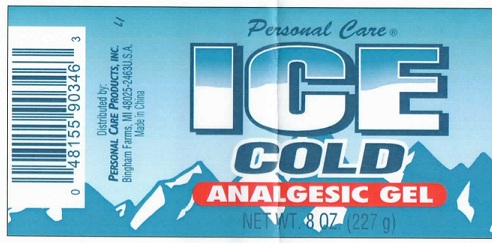 DRUG LABEL: Personal Care Ice Cold 
NDC: 29500-2278 | Form: GEL
Manufacturer: Personal Care Products, Inc.
Category: otc | Type: HUMAN OTC DRUG LABEL
Date: 20110825

ACTIVE INGREDIENTS: MENTHOL 1 g/100 g
INACTIVE INGREDIENTS: THYMOL; WATER; ISOPROPYL ALCOHOL; SODIUM HYDROXIDE

Personal Care Ice Cold Analgesic

DRUG FACTS

Active ingredients Purpose

Menthol (1%)................................Topical Analgesic

PURPOSE

Uses-For the temporary relief of minor aches and pains in muscles and joints associated with:

simple backache

sports injuries

strains

arthritis

sprains

bruises

warnings

For external use only

Do not use with other topical pain relievers

with heating pads or heating devices

When using this product

do not use in or near eyes

do not apply to wounds or damaged skin

do not bandage tightly

Stop use and ask a doctor if

condition worsens

symptoms last more than 7 days or clear up and occur again within a few days

redness or irritation develops

INDICATIONS AND USAGE

For the temporary relief of aches and pains in muscles and joints associated with

simple backache

sports injuries

strains

arthritis

sprains

bruises

Keep out of reach of children.

if swallowed, get medical help or contact a poison control center right away.

Directions

Clean affected area before applying product

adults and children 2 years of age and older: apply to affected area not more than 3 to 4 times daily.

INACTIVE INGREDIENT

Inactive Ingredients: carbomer, isopropyl alcohol, kathon CG, sodium hydroxide, thymol, water(aqua), FDandC blue no 1

PACKAGE LABEL

DISTRIBUTED BY PERSONAL CARE PRODUCTS INC

Bingham Farms MI 48025-2463 USA

Made in China

Personal Care Ice Cold Analgesic Gel

Net wt. 8oz (227g)